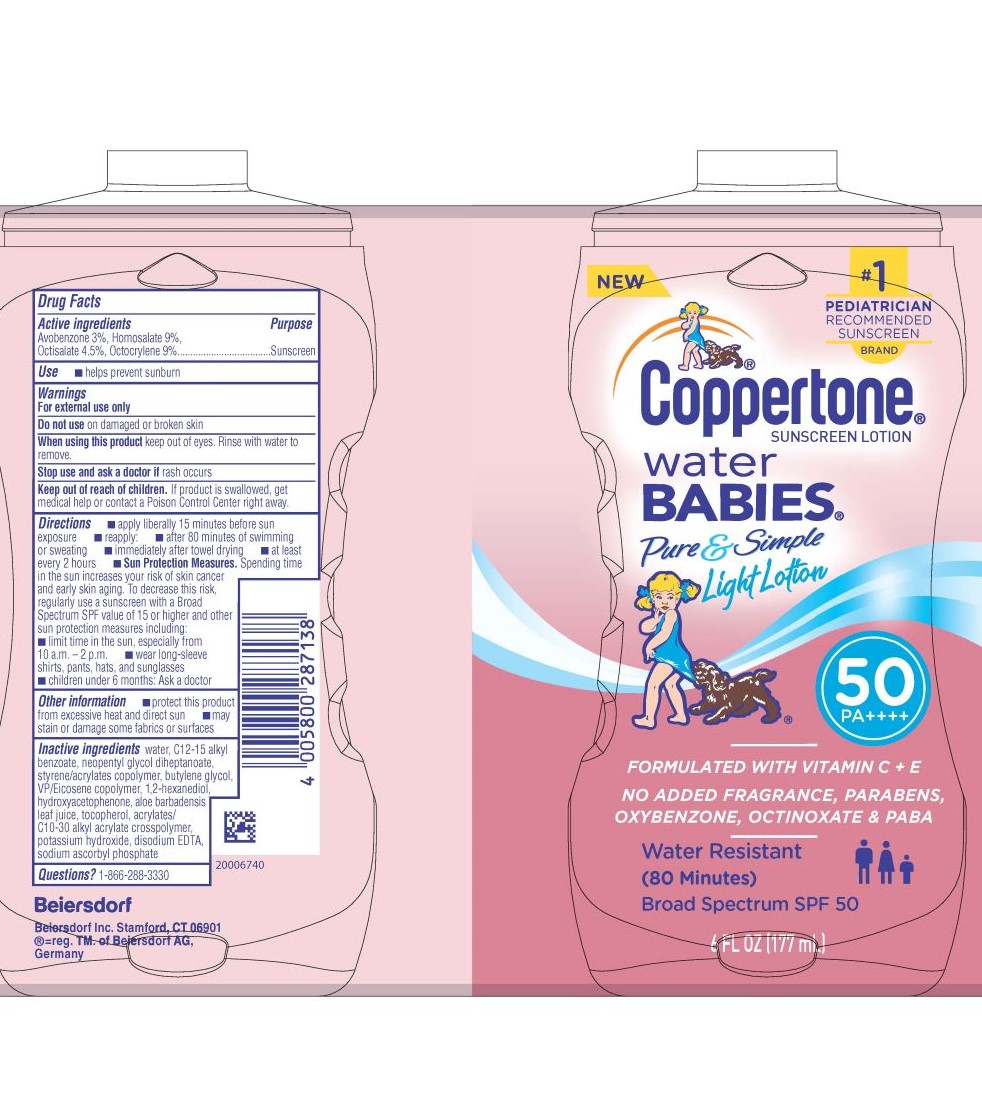 DRUG LABEL: Coppertone Waterbabies Pure and Simple Sunscreen SPF 50
NDC: 66800-4840 | Form: LOTION
Manufacturer: Beiersdorf Inc
Category: otc | Type: HUMAN OTC DRUG LABEL
Date: 20251231

ACTIVE INGREDIENTS: AVOBENZONE 3 g/100 g; HOMOSALATE 9 g/100 g; OCTISALATE 4.5 g/100 g; OCTOCRYLENE 9 g/100 g
INACTIVE INGREDIENTS: WATER; ALKYL (C12-15) BENZOATE; SODIUM ASCORBYL PHOSPHATE; ALOE VERA LEAF; CARBOMER INTERPOLYMER TYPE A (ALLYL SUCROSE CROSSLINKED); VINYLPYRROLIDONE/EICOSENE COPOLYMER; 1,2-HEXANEDIOL; HYDROXYACETOPHENONE; TOCOPHEROL; BUTYLENE GLYCOL; STYRENE/ACRYLAMIDE COPOLYMER (MW 500000); DISODIUM EDTA-COPPER; POTASSIUM HYDROXIDE; NEOPENTYL GLYCOL DIHEPTANOATE

Waterbabies Pure & Simple Light Lotion SPF 50 Sunscreen

Active ingredients

Avobenzone 3%, Homosalate 9%, Octisalate 4.5%, Octocrylene 9%

Purpose

Sunscreen

Use

■ helps prevent sunburn

Warnings

For external use only

Do not useon damaged or broken skin

WHEN USING

When using this productkeep out of eyes. Rinse with water to remove.

Stop use and ask a doctor ifrash occurs

Keep out of reach of children.If product is swallowed, get medical help or contact a Poison Control Center right away.

Directions

■ apply liberally 15 minutes before sun exposure

■ reapply:

■ after 80 minutes of swimming or sweating

■ immediately after towel drying

■ at least every 2 hours

■ Sun Protection Measures.Spending time in the sun increases your risk of skin cancer and early skin aging. To decrease this risk, regularly use a sunscreen with a Broad Spectrum SPF value of 15 or higher and other sun protection measures including:

■ limit time in the sun, especially from 10 a.m. – 2 p.m.

■ wear long-sleeve shirts, pants, hats, and sunglasses

■ children under 6 months: Ask a doctor

Other information

■ protect this product from excessive heat and direct sun

■ may stain or damage some fabrics or surfaces

Inactive ingredients

water, C12-15 alkyl benzoate, neopentyl glycol diheptanoate, styrene/acrylates copolymer, butylene glycol, VP/Eicosene copolymer, 1,2-hexanediol, hydroxyacetophenone, aloe barbadensis leaf juice,

tocopherol, acrylates/C10-30 alkyl acrylate crosspolymer, potassium hydroxide,

disodium EDTA, sodium ascorbyl phosphate

Questions?

1-866-288-3330

PACKAGE LABEL

NEW

#1 Pediatrician Recommended Sunscreen Brand
Coppertone® Sunscreen Lotion

water babies Pure&Simple Light Lotion

SPF50 PA++++

Formulated with Vitamin C + E

No Added Fragrance, Parabens, Oxybenzone, Octinoxate & PABA

Water Resistant (80 Minutes)

Broad Spectrum SPF 50

6 FL OZ (177 mL)